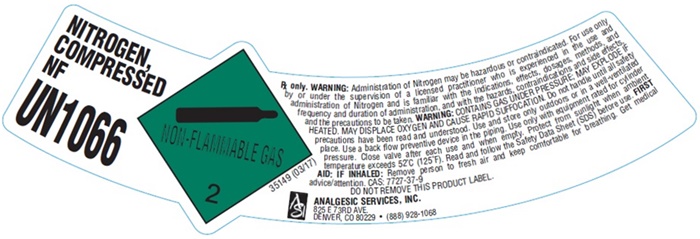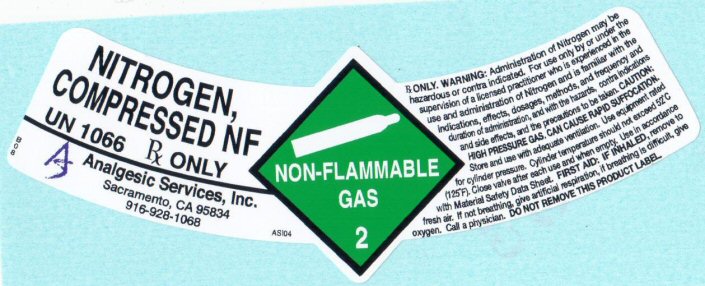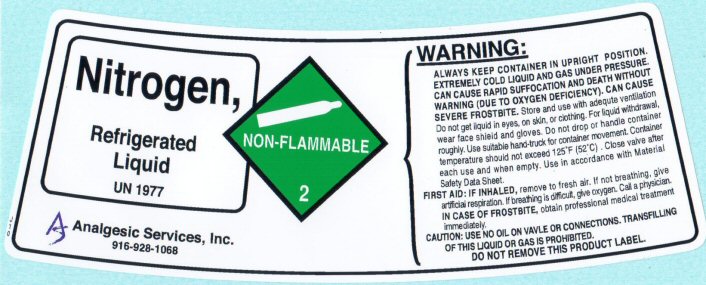 DRUG LABEL: NITROGEN
NDC: 52085-002 | Form: GAS
Manufacturer: ANALGESIC SERVICES, INC.
Category: prescription | Type: HUMAN PRESCRIPTION DRUG LABEL
Date: 20251029

ACTIVE INGREDIENTS: NITROGEN 99 L/100 L

Nitrogen

Product Label NITROGEN COMPRESSED NF - California

NITROGEN COMPRESSED NF

UN 1066 Rx ONLY

BO8

Analgesic Services, Inc.
Sacramento, CA 95834
916-928-1068

ASI04

NON-FLAMMABLE GAS 2

Rx ONLY. WARNING: Administration of Nitrogen may be hazardous or contraindicated. For use only by or under the supervision of a licensed practitioner who is experienced in the use and administration of Nitrogen and is familiar with the indications, effects, dosages, methods, and frequency and duration of administration, and with the hazards, contraindications, and side effects and the precautions to be taken.
CAUTION: HIGH PRESSURE GAS. CAN CAUSE RAPID SUFFOCATION.
Store and use with adequate ventilation. Use equipment rated for cylinder pressure.Cylinder temperature should not exceed 52 ° C (125 ° F). Close valve after each use and when empty. Use in accordance with the Material Safety Data Sheet (MSDS).
FIRST AID: IF INHALED, remove to fresh air. If not breathing, give artificial respiration. If breathing is difficult,give oxygen. Call a physician.
DO NOT REMOVE THIS PRODUCT LABEL

Product Label NITROGEN REFRIGERATED LIQUID - California

Nitrogen Refrigerated Liquid

UN 1977

J10

Analgesic Services, Inc.
916-928-1068

NON-FLAMMABLE 2

WARNING:
ALWAYS KEEP CONTAINER IN UPRIGHT POSITION. EXTREMELY COLD LIQUID AND GAS UNDER PRESSURE. CAN CAUSE RAPID SUFFOCATION AND DEATH WITHOUT WARNING (DUE TO OXYGEN DEFICIENCY). CAN CAUSE SEVERE FROSTBITE.

Store and use with adequate ventilation. Do not get liquid in eyes, on skin, or clothing. For liquid withdraw, wear face shield and gloves. Do not drop or handle container roughly. Use suitable hand-truck for container movement.Container temperature should not exceed 125° F (52° C). Close valve after each use and when empty. Use in accordance with the Material Safety Data Sheet (MSDS).
FIRST AID: IF INHALED, remove to fresh air. If not breathing, give artificial respiration. If breathing is difficult, give oxygen. Call a physician.
IN CASE OF FROSTBITE, obtain professional medical treatment immediately.

CAUTION: USE NO OIL ON VALVE OR CONNECTIONS. TRANSFILLING OF THIS LIQUID OR GAS IS PROHIBITED.
DO NOT REMOVE THIS PRODUCT LABEL.

Nitrogen Compressed NF - Denver

NITROGEN, COMPRESSED NF UN1066

NON-FLAMMABLE GAS 2 35149 (03/17)

Rx only. WARNING: Administration of Nitrogen may be hazardous or contraindicated. For use only by or under the supervision of a licensed practioner who is experienced in the use and administration of Nitrogen and is familiar with the indications, effects, dosages, methods, and frequency and duration of administration, and with the hazards, contraindications and side effects and the precautions to be taken. WARNING: CONTAINS GAS UNDER PRESSURE; MAY EXPLODE, IF HEATED, MAY DISPLACE OXYGEN AND CAUSE RAPID SUFFOCCATION. Do not handle until all safety precautions have been read and understood. Use and store only outdoors or in a well-ventilated place. Use a back flow preventive device in the piping. Use only with equipment rated for cylinder pressure. Close valve after each use and when empty. Protect from sunlight when ambient temperature exceeds 52°C (125°F). Read and follow the Safety Data Sheet (SDS) before use. FIRST AID: IF INHALED: Remove person to fresh air and keep comfortable for breathing. Get medical advice/attention. CAS: 7727-37-9

DO NOT REMOVE THIS PRODUCT LABEL

ANALGESIC SERVICES, INC.

825 e 73RD AVE.

DENVER, CO 80229 • (888) 928-1068